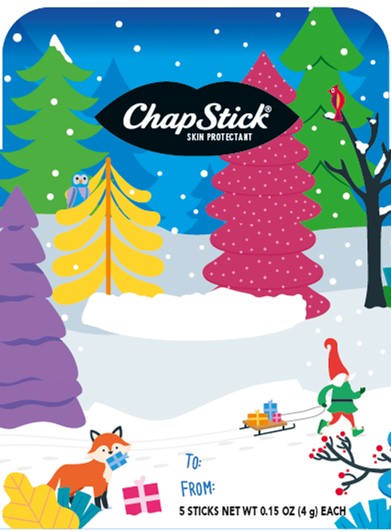 DRUG LABEL: Chapstick Holiday Classics Kit
NDC: 0573-0805 | Form: KIT | Route: TOPICAL
Manufacturer: Haleon US Holdings LLC
Category: otc | Type: HUMAN OTC DRUG LABEL
Date: 20240411

ACTIVE INGREDIENTS: PETROLATUM 450 mg/1 g; PETROLATUM 450 mg/1 g; PETROLATUM 450 mg/1 g; PETROLATUM 450 mg/1 g
INACTIVE INGREDIENTS: ARACHIDYL PROPIONATE; CAMPHOR (NATURAL); CARNAUBA WAX; CETYL ALCOHOL; ISOPROPYL MYRISTATE; LANOLIN; LIGHT MINERAL OIL; OCTYLDODECANOL; OLEYL ALCOHOL; PARAFFIN; PHENYL TRIMETHICONE; D&C RED NO. 6; TITANIUM DIOXIDE; WHITE WAX; FD&C YELLOW NO. 5; ARACHIDYL PROPIONATE; CAMPHOR (NATURAL); CARNAUBA WAX; CETYL ALCOHOL; ISOPROPYL MYRISTATE; LANOLIN; LEMON OIL, COLD PRESSED; LIGHT MINERAL OIL; MALTOL; OCTYLDODECANOL; PARAFFIN; PHENYL TRIMETHICONE; D&C RED NO. 6; SACCHARIN; WHITE WAX; ARACHIDYL PROPIONATE; CAMPHOR (NATURAL); CARNAUBA WAX; CETYL ALCOHOL; ISOPROPYL MYRISTATE; LANOLIN; LIGHT MINERAL OIL; LEVOMENTHOL; OCTYLDODECANOL; PARAFFIN; PHENYL TRIMETHICONE; D&C RED NO. 6; SACCHARIN; WHITE WAX; ARACHIDYL PROPIONATE; FD&C BLUE NO. 1; CARNAUBA WAX; CETYL ALCOHOL; ISOPROPYL MYRISTATE; LANOLIN; LIGHT MINERAL OIL; MALTOL; OCTYLDODECANOL; PARAFFIN; PHENYL TRIMETHICONE; SACCHARIN; WHITE WAX; FD&C YELLOW NO. 5

Drug Facts

Active ingredient

White petrolatum 45%

Purpose

Skin Protectant

Uses

- helps prevent and temporarily protects chafed, chapped or cracked lips
- helps prevent and protect from the drying effects of wind and cold weather

Warnings

For external use only

Keep Out of Reach of Children

If swallowed, get medical help or contact a Poison Control Center right away.

Directions

apply as needed

Other information

store at 20-25°C (68-77°F)

Inactive ingredients

arachidyl propionate, *blue 1 lake, *camphor, carnauba wax, cetyl alcohol, *fragrance, isopropyl lanolate, isopropyl myristate, lanolin, *lemon oil, light mineral oil, *maltol, *menthol, *natural and artificial flavor, octyldodecanol, *oleyl alcohol, paraffin, phenyl trimethicone, *red 6 lake, *saccharin, *titanium dioxide, white wax, *yellow 5 lake

*contains one or more of these ingredients

Questions or Comments?

Call weekdays from 9 AM to 6 PM EST at 1-800-245-1040

Additional Information

Paraben Free

Dist. by: GSK CH, Warren, NJ 07059

For most recent product information, visit www.chapstick.com

Questions or Comments? 1-800-245-1040

Trademarks owned or licensed by GSK.

©2023 GSK or licensor.

203531

PRINCIPAL DISPLAY PANEL

ChapStick®

SKIN PROTECTANT

TO:

FROM:

5 STICKS

NET WT 0.15 OZ
(4 g) EACH

203531 – Front Panel